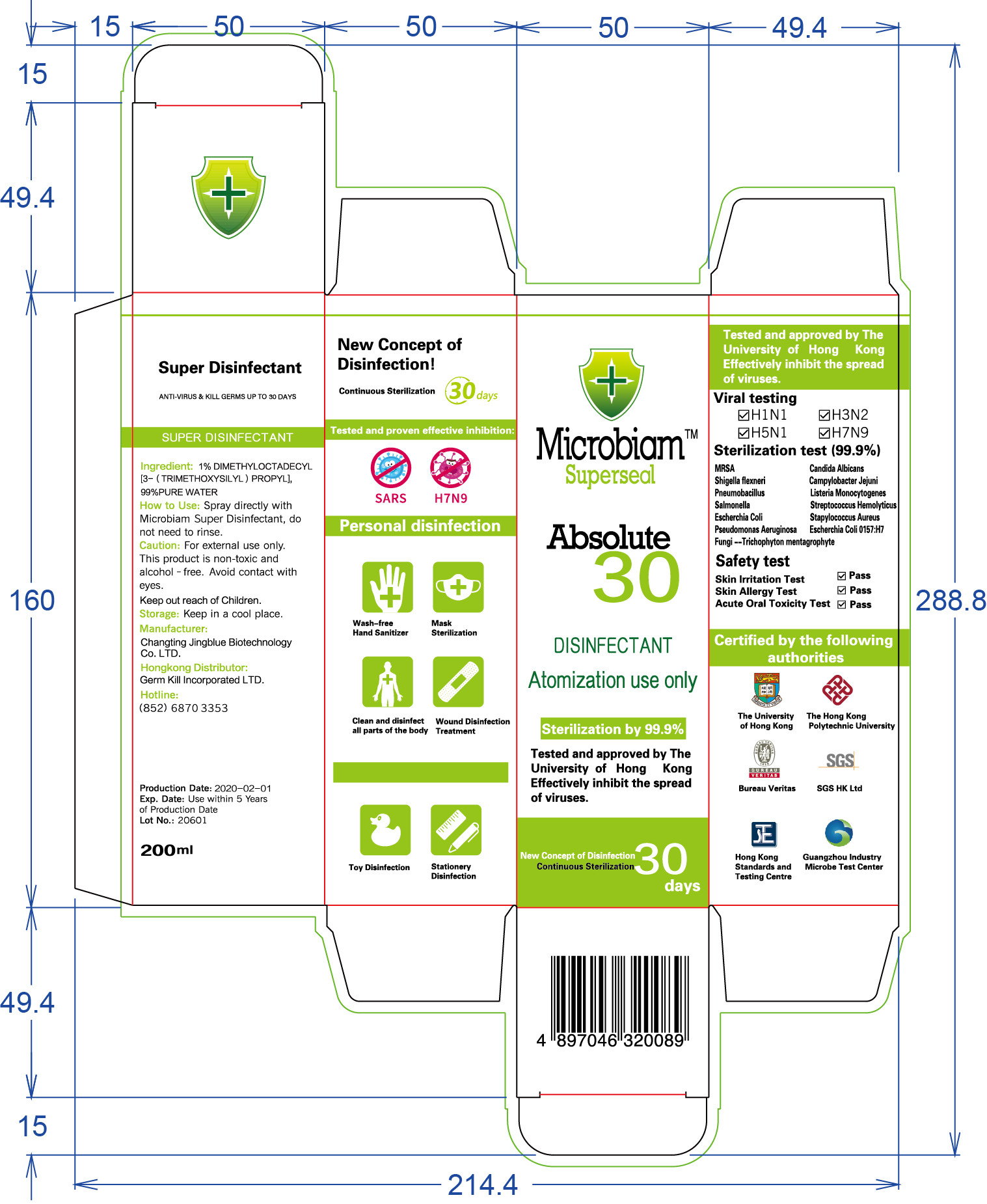 DRUG LABEL: Microbiam Super Disinfectant
NDC: 55668-001 | Form: LIQUID
Manufacturer: Changting JINGBLUE Biotechnology Co., Ltd.
Category: otc | Type: HUMAN OTC DRUG LABEL
Date: 20201022

ACTIVE INGREDIENTS: DIMETHYLOCTADECYL(3-(TRIMETHOXYSILYL)PROPYL)AMMONIUM 2 g/200 mL
INACTIVE INGREDIENTS: WATER

DOSAGE AND ADMINISTRATION

Keep in a cool place.

INACTIVE INGREDIENT

Pure Water

INDICATIONS AND USAGE

Spray directly withMicrobiam Super Disinfectant, do not need to rinse.

ACTIVE INGREDIENT

DIMETHYLOCTADECYL[3-（TRIMETHOXYSILYL）PROPYL]

keep out of reach of children

PURPOSE

Disinfection
Sterilization
No Rinseing

WARNINGS

For external use only.This product is non-toxic andalcohol - free.Avoid contact witheyes.